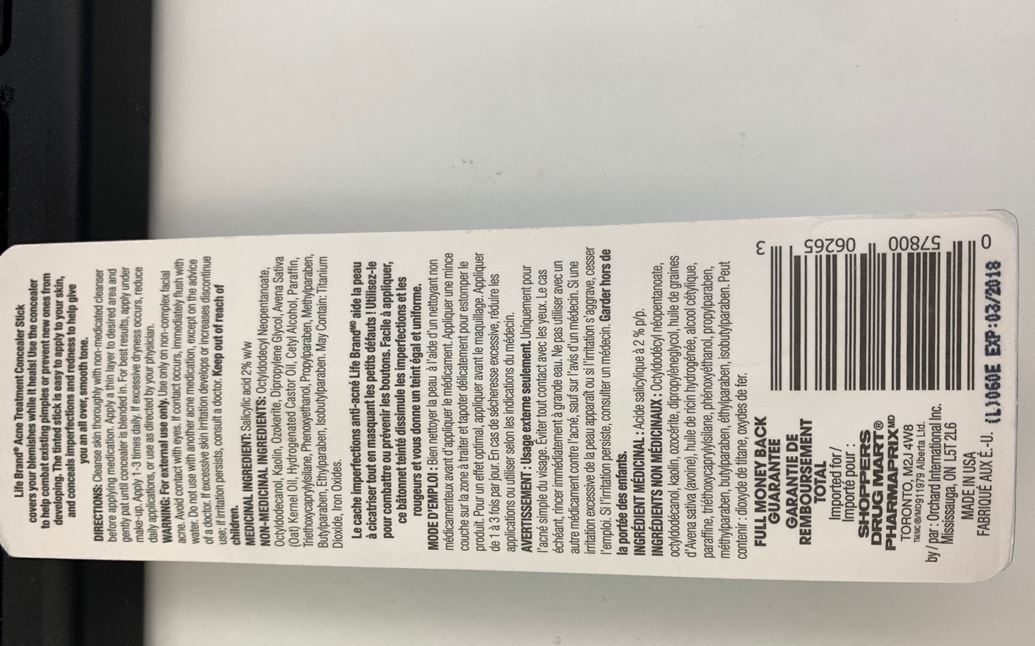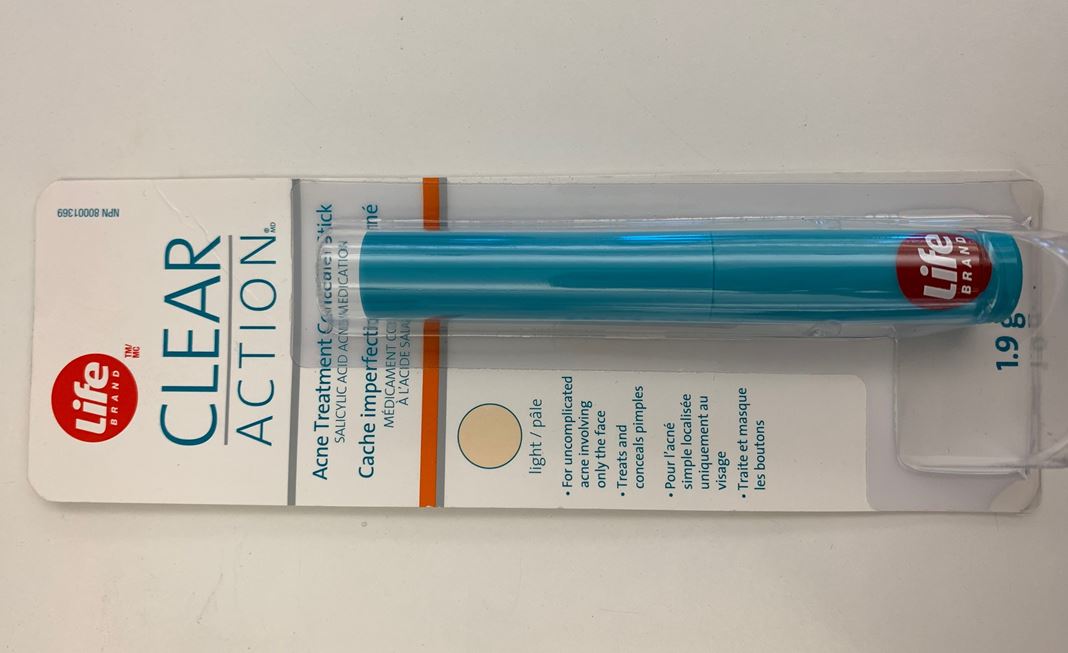 DRUG LABEL: cream
NDC: 61354-060 | Form: STICK
Manufacturer: Oxygen Development LLC
Category: otc | Type: HUMAN OTC DRUG LABEL
Date: 20210223

ACTIVE INGREDIENTS: SALICYLIC ACID 2 mg/100 mg
INACTIVE INGREDIENTS: CERESIN; DIPROPYLENE GLYCOL; HYDROGENATED CASTOR OIL; PARAFFIN; OAT KERNEL OIL; CETYL ALCOHOL; OCTYLDODECANOL; KAOLIN; OCTYLDODECYL NEOPENTANOATE

LIFE BRAND CLEAR ACTION ACNE TREATMENT CONCEALER STICK SALICYLIC ACID ACNE MEDICATION

Directions

Cleanse skin thoroughly with non-medicated cleanser before applying medication. Apply a thin layer to desired area and gently pat until concealer is blended in. For best results, apply under make-up. Apply 1-3 times daily. If excessive dryness occurs, reduce daily applications, or use as directed by your physician.

Warning

For external use only. Use only on non-complex facial acne. Avoid contact with eyes. If contact occurs, immediately flush with water. Do not use with another acne medication, except on the advice of a doctor. If excessive skin irritation develops or increases discontinue use; if irritation persists, consult a doctor.

Medicinal Ingredient

Salicylic Acid 2% w/w

Non-Medicinal Ingredients

Octyldodecyl Neopentanoate, Octyldodecanol, Kaolin, Ozokerite, Dipropylene Glycol, Avena Sativa (Oat) Kernel Oil, Hydrogenated Castor Oil, Cetyl Alcohol, Paraffin, Triethoxycaprylylsilane, Phenoxyethanol, Propylparaben, Methylparaben, Butylparaben, Ethylparaben, Isobutylparaben. May Contain: Titanium Dioxide, Iron Oxides.

Keep out of reach of children.

PURPOSE

Anti-Acne

INDICATIONS AND USAGE

Use the concealer to help combat existing pimples or prevent new ones from developing.